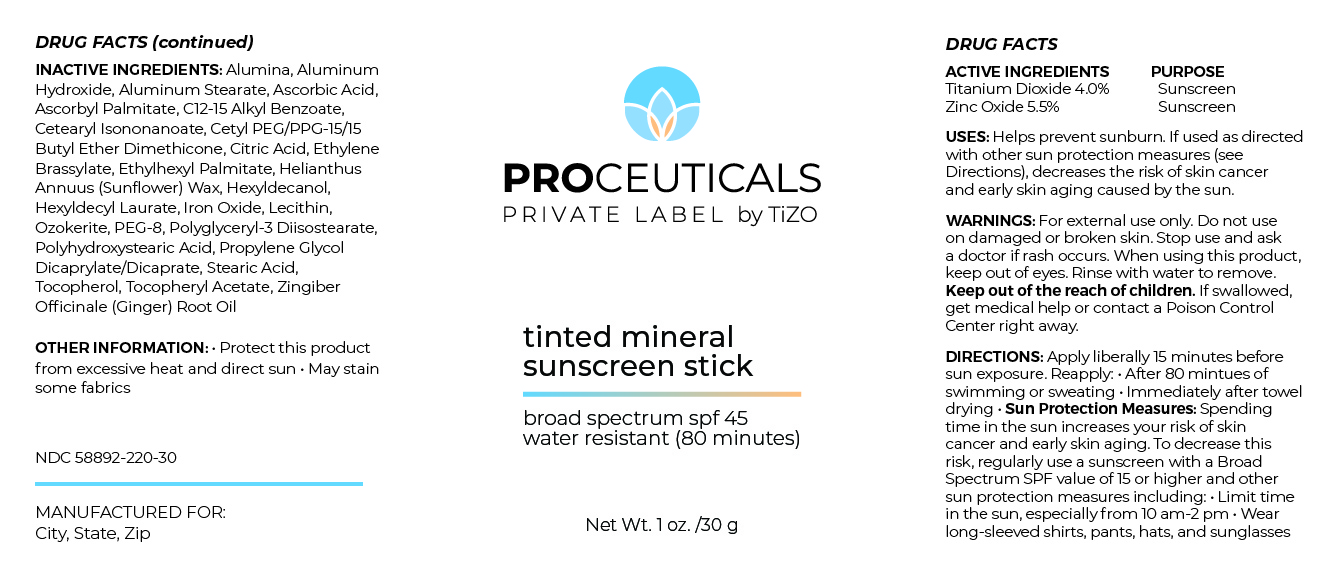 DRUG LABEL: Proceuticals Private Label by TiZO tinted mineral sunscreen stick
NDC: 58892-220 | Form: STICK
Manufacturer: Fallien Cosmeceuticals, Ltd
Category: otc | Type: HUMAN OTC DRUG LABEL
Date: 20240906

ACTIVE INGREDIENTS: TITANIUM DIOXIDE 40 mg/1 g; ZINC OXIDE 55 mg/1 g
INACTIVE INGREDIENTS: ALKYL (C12-15) BENZOATE; HELIANTHUS ANNUUS SEED WAX; CERESIN; TOCOPHEROL; HEXYLDECANOL; POLYETHYLENE GLYCOL 400; CETYL PEG/PPG-10/1 DIMETHICONE (HLB 4); ETHYLHEXYL PALMITATE; POLYGLYCERYL-3 DIISOSTEARATE; POLYHYDROXYSTEARIC ACID (2300 MW); ASCORBYL PALMITATE; ETHYLENE BRASSYLATE; .ALPHA.-TOCOPHEROL ACETATE; HEXYL LAURATE; ASCORBIC ACID; CETEARYL ISONONANOATE; ALUMINUM STEARATE; CITRIC ACID MONOHYDRATE; DIPROPYLENE GLYCOL CAPRYLATE; GINGER OIL; ALUMINUM OXIDE; ALUMINUM HYDROXIDE; LECITHIN, SUNFLOWER; STEARIC ACID; FERRIC OXIDE RED

ACTIVE INGREDIENTS:

Titanium Dioxide 4.0%

Zinc Oxide 5.5%

PURPOSE:Sunscreen

USES: Helps prevent sunburn. If used as directed
with other sun protection measures (see
Directions), decreases the risk of skin cancer
and early skin aging caused by the sun.

INDICATIONS AND USAGE

DIRECTIONS:DIRECTIONS: Apply liberally 15 minutes before
sun exposure. Reapply: • After 80 mintues of
swimming or sweating • Immediately after towel
drying • Sun Protection Measures: Spending
time in the sun increases your risk of skin
cancer and early skin aging. To decrease this
risk, regularly use a sunscreen with a Broad
Spectrum SPF value of 15 or higher and other
sun protection measures including: • Limit time
in the sun, especially from 10 am-2 pm • Wear
long-sleeved shirts, pants, hats, and sunglasses

INACTIVE INGREDIENTS: Alumina, Aluminum
Hydroxide, Aluminum Stearate, Ascorbic Acid,
Ascorbyl Palmitate, C12-15 Alkyl Benzoate,
Cetearyl Isononanoate, Cetyl PEG/PPG-15/15
Butyl Ether Dimethicone, Citric Acid, Ethylene
Brassylate, Ethylhexyl Palmitate, Helianthus
Annuus (Sunflower) Wax, Hexyldecanol,
Hexyldecyl Laurate, Iron Oxide, Lecithin,
Ozokerite, PEG-8, Polyglyceryl-3 Diisostearate,
Polyhydroxystearic Acid, Propylene Glycol
Dicaprylate/Dicaprate, Stearic Acid,
Tocopherol, Tocopheryl Acetate, Zingiber
Officinale (Ginger) Root Oil

OTHER INFORMATION: • Protect this product
from excessive heat and direct sun • May stain
some fabrics

WARNINGS: For external use only. Do not use
on damaged or broken skin. Stop use and ask
a doctor if rash occurs. When using this product,
keep out of eyes. Rinse with water to remove.
Keep out of the reach of children. If swallowed,
get medical help or contact a Poison Control
Center right away.

Keep out of the reach of children.

DOSAGE AND ADMINISTRATION

Helps prevent sunburn. If used as directed
with other sun protection measures (see
Directions), decreases the risk of skin cancer
and early skin aging caused by the sun.

Apply liberally 15 minutes befor sun exposure.

Principal Display Panel – 30g Cylinder Label

PROCEUTICALS

PRIVATE LABEL by TiZO

tinted mineral

sunscreen stick

broad spectrum spf 45
water resistant (80 minutes)

Net Wt. 1 oz. /30 g

Graphic-Untitled